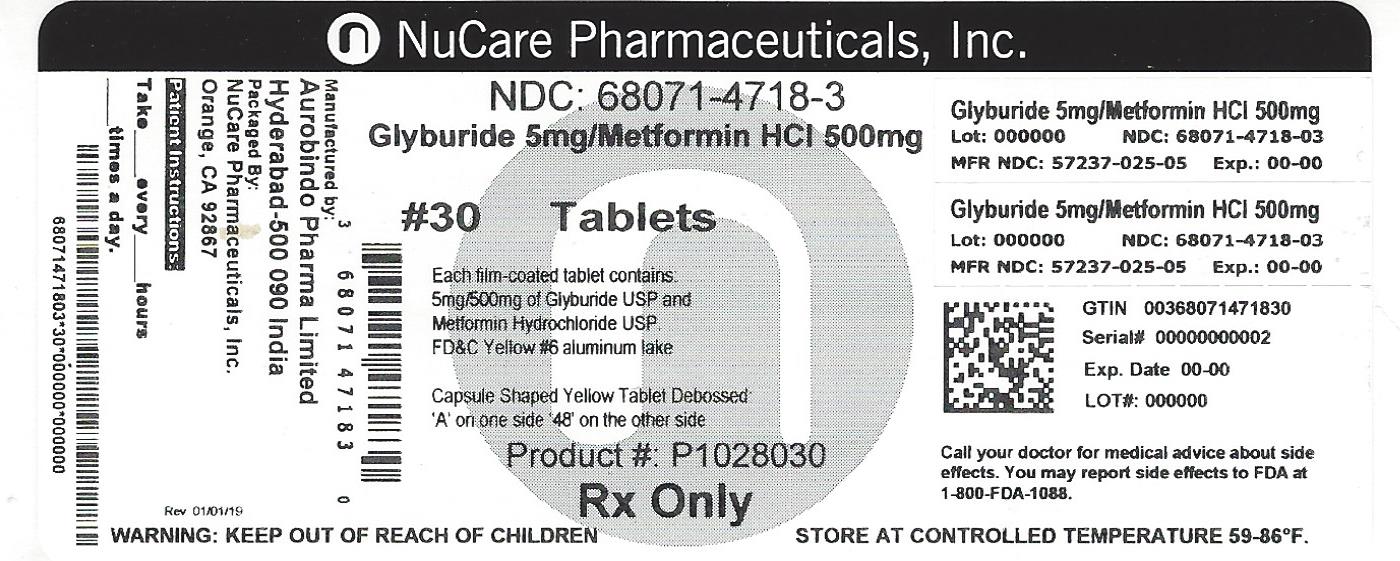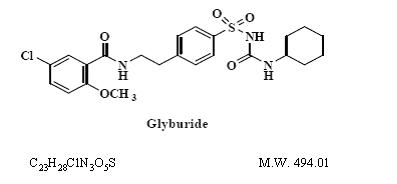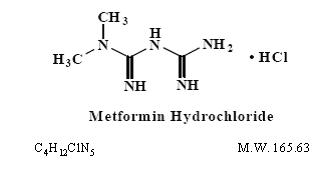 DRUG LABEL: Glyburide and Metformin Hydrochloride
NDC: 68071-4718 | Form: TABLET, FILM COATED
Manufacturer: NuCare Pharmaceuticals,Inc.
Category: prescription | Type: HUMAN PRESCRIPTION DRUG LABEL
Date: 20240612

ACTIVE INGREDIENTS: GLYBURIDE 5 mg/1 1; METFORMIN HYDROCHLORIDE 500 mg/1 1
INACTIVE INGREDIENTS: CELLULOSE, MICROCRYSTALLINE; CROSCARMELLOSE SODIUM; POVIDONE K90; MAGNESIUM STEARATE; HYPROMELLOSE 2910 (6 MPA.S); PROPYLENE GLYCOL; POLYSORBATE 80; TALC; TITANIUM DIOXIDE; FD&C YELLOW NO. 6; D&C YELLOW NO. 10

Glyburide and Metformin Hydrochloride Tablets, USP
Rx only

DESCRIPTION

Glyburide and metformin hydrochloride tablets, USP contain 2 oral antihyperglycemic drugs used in the management of type 2 diabetes, glyburide USP and metformin hydrochloride USP.
Glyburide USP is an oral antihyperglycemic drug of the sulfonylurea class. The chemical name for glyburide is 1-[[ p-[2-(5-chloro- o-anisamido)ethyl]phenyl]sulfonyl]-3-cyclo-hexylurea. Glyburide USP is a white to off-white crystalline compound. The structural formula is represented below.

Metformin hydrochloride USP is an oral antihyperglycemic drug used in the management of type 2 diabetes. Metformin hydrochloride (N, N-dimethylimidodicarbonimidic diamide monohydrochloride) is not chemically or pharmacologically related to sulfonylureas, thiazolidinediones, or α-glucosidase inhibitors. It is a white to off-white crystalline compound. Metformin hydrochloride is freely soluble in water and is practically insoluble in acetone, ether, and chloroform. The pKa of metformin is 12.4. The pH of a 1% aqueous solution of metformin hydrochloride is 6.68. The structural formula is as shown:

Glyburide and metformin hydrochloride tablets, USP are available for oral administration containing 1.25 mg glyburide USP with 250 mg metformin hydrochloride USP, 2.5 mg glyburide USP with 500 mg metformin hydrochloride USP, and 5 mg glyburide USP with 500 mg metformin hydrochloride USP. In addition, each film-coated tablet contains the following inactive ingredients: microcrystalline cellulose, croscarmellose sodium, povidone, magnesium stearate, hypromellose, propylene glycol, polysorbate 80, talc, titanium dioxide and FD&C Yellow#6 aluminum lake. The 1.25 mg/250 mg and 5 mg/500 mg strengths also contain D&C Yellow#10 aluminum lake; The 2.5 mg/500 mg strength also contains FD&C Red#40 aluminum lake.
Meets USP Dissolution Test 2

CLINICAL PHARMACOLOGY

Mechanism of Action

Glyburide and metformin hydrochloride tablets combine glyburide and metformin hydrochloride, 2 antihyperglycemic agents with complementary mechanisms of action, to improve glycemic control in patients with type 2 diabetes.
Glyburide appears to lower blood glucose acutely by stimulating the release of insulin from the pancreas, an effect dependent upon functioning beta cells in the pancreatic islets. The mechanism by which glyburide lowers blood glucose during long-term administration has not been clearly established. With chronic administration in patients with type 2 diabetes, the blood glucose-lowering effect persists despite a gradual decline in the insulin secretory response to the drug. Extrapancreatic effects may be involved in the mechanism of action of oral sulfonylurea hypoglycemic drugs.
Metformin hydrochloride is an antihyperglycemic agent that improves glucose tolerance in patients with type 2 diabetes, lowering both basal and postprandial plasma glucose. Metformin hydrochloride decreases hepatic glucose production, decreases intestinal absorption of glucose, and improves insulin sensitivity by increasing peripheral glucose uptake and utilization.

Pharmacokinetics

Absorption and Bioavailability

Glyburide and Metformin Hydrochloride

In bioavailability studies of glyburide and metformin hydrochloride 2.5 mg/500 mg and 5 mg/500 mg, the mean area under the plasma concentration versus time curve (AUC) for the glyburide component was 18% and 7%, respectively, greater than that of the MICRONASE® brand of glyburide co-administered with metformin. The glyburide component of glyburide and metformin hydrochloride, therefore, is not bioequivalent to MICRONASE®. The metformin component of glyburide and metformin hydrochloride is bioequivalent to metformin coadministered with glyburide.

Following administration of a single glyburide and metformin hydrochloride 5 mg/500 mg tablet with either a 20% glucose solution or a 20% glucose solution with food, there was no effect of food on the Cmax and a relatively small effect of food on the AUC of the glyburide component. The Tmax for the glyburide component was shortened from 7.5 hours to 2.75 hours with food compared to the same tablet strength administered fasting with a 20% glucose solution. The clinical significance of an earlier Tmax for glyburide after food is not known. The effect of food on the pharmacokinetics of the metformin component was indeterminate.

Glyburide

Single-dose studies with MICRONASE® tablets in normal subjects demonstrate significant absorption of glyburide within 1 hour, peak drug levels at about 4 hours, and low but detectable levels at 24 hours. Mean serum levels of glyburide, as reflected by areas under the serum concentration-time curve, increase in proportion to corresponding increases in dose. Bioequivalence has not been established between glyburide and metformin hydrochloride tablets and single-ingredient glyburide products.

Metformin Hydrochloride

The absolute bioavailability of a 500 mg metformin hydrochloride tablet given under fasting conditions is approximately 50% to 60%. Studies using single oral doses of metformin tablets of 500 mg and 1500 mg, and 850 mg to 2550 mg, indicate that there is a lack of dose proportionality with increasing doses, which is due to decreased absorption rather than an alteration in elimination. Food decreases the extent of and slightly delays the absorption of metformin, as shown by approximately a 40% lower peak concentration and a 25% lower AUC in plasma and a 35-minute prolongation of time to peak plasma concentration following administration of a single 850 mg tablet of metformin with food, compared to the same tablet strength administered fasting. The clinical relevance of these decreases is unknown.

Distribution

Glyburide

Sulfonylurea drugs are extensively bound to serum proteins. Displacement from protein binding sites by other drugs may lead to enhanced hypoglycemic action. In vitro, the protein binding exhibited by glyburide is predominantly non-ionic, whereas that of other sulfonylureas (chlorpropamide, tolbutamide, tolazamide) is predominantly ionic. Acidic drugs, such as phenylbutazone, warfarin, and salicylates, displace the ionic-binding sulfonylureas from serum proteins to a far greater extent than the non-ionic binding glyburide. It has not been shown that this difference in protein binding results in fewer drug-drug interactions with glyburide tablets in clinical use.

Metformin Hydrochloride

The apparent volume of distribution (V/F) of metformin following single oral doses of 850 mg averaged 654±358 L. Metformin is negligibly bound to plasma proteins. Metformin partitions into erythrocytes, most likely as a function of time. At usual clinical doses and dosing schedules of metformin, steady-state plasma concentrations of metformin are reached within 24 to 48 hours and are generally <1 mcg/mL. During controlled clinical trials, maximum metformin plasma levels did not exceed 5 mcg/mL, even at maximum doses.

Metabolism and Elimination

Glyburide
The decrease of glyburide in the serum of normal healthy individuals is biphasic; the terminal half-life is about 10 hours. The major metabolite of glyburide is the 4-trans-hydroxy derivative. A second metabolite, the 3-cis-hydroxy derivative, also occurs. These metabolites probably contribute no significant hypoglycemic action in humans since they are only weakly active (1/400 and 1/40 as active, respectively, as glyburide) in rabbits. Glyburide is excreted as metabolites in the bile and urine, approximately 50% by each route. This dual excretory pathway is qualitatively different from that of other sulfonylureas, which are excreted primarily in the urine.
Metformin Hydrochloride
Intravenous single-dose studies in normal subjects demonstrate that metformin is excreted unchanged in the urine and does not undergo hepatic metabolism (no metabolites have been identified in humans) nor biliary excretion. Renal clearance (see Table 1) is approximately 3.5 times greater than creatinine clearance, which indicates that tubular secretion is the major route of metformin elimination. Following oral administration, approximately 90% of the absorbed drug is eliminated via the renal route within the first 24 hours, with a plasma elimination half-life of approximately 6.2 hours. In blood, the elimination half-life is approximately 17.6 hours, suggesting that the erythrocyte mass may be a compartment of distribution.

Specific Populations

Patients With Type 2 Diabetes
Multiple-dose studies with glyburide in patients with type 2 diabetes demonstrate drug level concentration-time curves similar to single-dose studies, indicating no buildup of drug in tissue depots.
In the presence of normal renal function, there are no differences between single- or multiple-dose pharmacokinetics of metformin between patients with type 2 diabetes and normal subjects (see Table 1), nor is there any accumulation of metformin in either group at usual clinical doses.
Hepatic Impairment
No pharmacokinetic studies have been conducted in patients with hepatic insufficiency for either glyburide or metformin (see PRECAUTIONS).
Renal Impairment
No information is available on the pharmacokinetics of glyburide in patients with renal insufficiency.
In patients with decreased renal function the plasma and blood half-life of metformin is prolonged and the renal clearance is decreased (see Table 1; also, see CONTRAINDICATIONS, WARNINGS, PRECAUTIONS, and DOSAGE AND ADMINISTRATION).
Geriatrics
There is no information on the pharmacokinetics of glyburide in elderly patients.
Limited data from controlled pharmacokinetic studies of metformin in healthy elderly subjects suggest that total plasma clearance is decreased, the half-life is prolonged, and Cmax is increased, when compared to healthy young subjects. From these data, it appears that the change in metformin pharmacokinetics with aging is primarily accounted for by a change in renal function (see Table 1; also see WARNINGS, PRECAUTIONS, and

DOSAGE AND ADMINISTRATION).

Table 1: Select Mean (±SD) Metformin Pharmacokinetic Parameters Following Single or Multiple Oral Doses of Metformin
Subject Groups: Metformin Dosea (number of subjects) | Cmaxb (mcg/mL) | Tmaxc (hrs) | Renal Clearance (mL/min)
Healthy, nondiabetic adults: 500 mg SDd (24) 850 mg SD (74)e 850 mg t.i.d. for 19 dosesf (9) | 1.03 (±0.33) 1.6 (±0.38) 2.01 (±0.42) | 2.75 (±0.81) 2.64 (±0.82) 1.79 (±0.94) | 600 (±132) 552 (±139) 642 (±173)
Adults with type 2 diabetes: 850 mg SD (23) 850 mg t.i.d. for 19 dosesf (9) | 1.48 (±0.5) 1.9 (±0.62) | 3.32 (±1.08) 2.01 (±1.22) | 491 (±138) 550 (±160)
Elderlyg, healthy nondiabetic adults: 850 mg SD (12) | 2.45 (±0.7) | 2.71 (±1.05) | 412 (±98)
Renal-impaired adults: 850 mg SD Mild (CLcrh 61 to 90 mL/min) (5) Moderate (CLcr 31 to 60 mL/min) (4) Severe (CLcr 10 to 30 mL/min) (6) | 1.86 (±0.52) 4.12 (±1.83) 3.93 (±0.92) | 3.2 (±0.45) 3.75 (±0.5) 4.01 (±1.1) | 384 (±122) 108 (±57) 130 (±90)
a All doses given fasting except the first 18 doses of the multiple-dose studies
b Peak plasma concentration
c Time to peak plasma concentration
d SD=single dose
e Combined results (average means) of 5 studies: mean age 32 years (range 23 to 59 years)
f Kinetic study done following dose 19, given fasting
g Elderly subjects, mean age 71 years (range 65 to 81 years)
h CLcr=creatinine clearance normalized to body surface area of 1.73 m^2

Pediatrics
After administration of a single oral metformin hydrochloride 500 mg tablet with food, geometric mean metformin Cmax and AUC differed <5% between pediatric type 2 diabetic patients (12 to 16 years of age) and gender- and weight-matched healthy adults (20 to 45 years of age), all with normal renal function.
After administration of a single oral glyburide and metformin hydrochloride tablet with food, dose-normalized geometric mean glyburide Cmax and AUC in pediatric patients with type 2 diabetes (11 to 16 years of age, n=28, mean body weight of 97 kg) differed <6% from historical values in healthy adults.
Gender
There is no information on the effect of gender on the pharmacokinetics of glyburide.
Metformin pharmacokinetic parameters did not differ significantly in subjects with or without type 2 diabetes when analyzed according to gender (males=19, females=16). Similarly, in controlled clinical studies in patients with type 2 diabetes, the antihyperglycemic effect of metformin was comparable in males and females.
Race
No information is available on race differences in the pharmacokinetics of glyburide.
No studies of metformin pharmacokinetic parameters according to race have been performed. In controlled clinical studies of metformin in patients with type 2 diabetes, the antihyperglycemic effect was comparable in whites (n=249), blacks (n=51), and Hispanics (n=24).

Clinical Studies

Patients with Inadequate Glycemic Control on Diet and Exercise Alone

In a 20-week, double-blind, multicenter U.S. clinical trial, a total of 806 drug-naive patients with type 2 diabetes, whose hyperglycemia was not adequately controlled with diet and exercise alone (baseline fasting plasma glucose [FPG] <240 mg/dL, baseline hemoglobin A1c [HbA1c] between 7% and 11%), were randomized to receive initial therapy with placebo, 2.5 mg glyburide, 500 mg metformin, glyburide and metformin hydrochloride 1.25 mg/250 mg, or glyburide and metformin hydrochloride 2.5 mg/500 mg. After 4 weeks, the dose was progressively increased (up to the 8-week visit) to a maximum of 4 tablets daily as needed to reach a target FPG of 126 mg/dL. Trial data at 20 weeks are summarized in Table 2.

Table 2: Placebo- and Active-Controlled Trial of Glyburide and Metformin Hydrochloride in Patients with Inadequate Glycemic Control on Diet and Exercise Alone: Summary of Trial Data at 20 Weeks
 | Placebo | Glyburide 2.5 mg Tablets | Metformin 500 mg Tablets | Glyburide and Metformin Hydrochloride 1.25 mg/250 mg Tablets | Glyburide and Metformin Hydrochloride 2.5 mg/500 mg Tablets
Mean Final Dose | 0 mg | 5.3 mg | 1317 mg | 2.78 mg/557 mg | 4.1 mg/824 mg
Hemoglobin A1c | N=147 | N=142 | N=141 | N=149 | N=152
Baseline Mean (%) | 8.14 | 8.14 | 8.23 | 8.22 | 8.2
Mean Change from Baseline | -0.21 | -1.24 | -1.03 | -1.48 | -1.53
Difference from Placebo |  | -1.02 | -0.82 | -1.26a | -1.31a
Difference from Glyburide |  |  |  | -0.24b | -0.29b
Difference from Metformin |  |  |  | -0.44b | -0.49b
Fasting Plasma Glucose | N=159 | N=158 | N=156 | N=153 | N=154
Baseline Mean FPG (mg/dL) | 177.2 | 178.9 | 175.1 | 178 | 176.6
Mean Change from Baseline | 4.6 | -35.7 | -21.2 | -41.5 | -40.1
Difference from Placebo |  | -40.3 | -25.8 | -46.1a | -44.7a
Difference from Glyburide |  |  |  | -5.8c | -4.5c
Difference from Metformin |  |  |  | -20.3c | -18.9c
Body Weight Mean Change from Baseline | -0.7 kg | +1.7 kg | -0.6 kg | +1.4 kg | +1.9 kg
Final HbA1c Distribution (%) | N=147 | N=142 | N=141 | N=149 | N=152
<7% | 19.7% | 59.9% | 50.4% | 66.4% | 71.7%
≥7% and <8% | 37.4% | 26.1% | 29.8% | 25.5% | 19.1%
≥8% | 42.9% | 14.1% | 19.9% | 8.1% | 9.2%
a p<0.001
b p<0.05
c p=NS

Treatment with glyburide and metformin hydrochloride resulted in significantly greater reduction in HbA1c and postprandial plasma glucose (PPG) compared to glyburide, metformin, or placebo. Also, glyburide and metformin hydrochloride therapy resulted in greater reduction in FPG compared to glyburide, metformin, or placebo, but the differences from glyburide and metformin did not reach statistical significance.
Changes in the lipid profile associated with glyburide and metformin hydrochloride treatment were similar to those seen with glyburide, metformin, and placebo.
The double-blind, placebo-controlled trial described above restricted enrollment to patients with HbA1c <11% or FPG <240 mg/dL. Screened patients ineligible for the first trial because of HbA1c and/or FPG exceeding these limits were treated directly with glyburide and metformin hydrochloride 2.5 mg/500 mg in an open-label, uncontrolled protocol. In this study, 3 out of 173 patients (1.7%) discontinued because of inadequate therapeutic response. Across the group of 144 patients who completed 26 weeks of treatment, mean HbA1c was reduced from a baseline of 10.6% to 7.1%. The mean baseline FPG was 283 mg/dL and reduced to 164 and 161 mg/dL after 2 and 26 weeks, respectively. The mean final titrated dose of glyburide and metformin hydrochloride was 7.85 mg/1569 mg (equivalent to approximately 3 glyburide and metformin hydrochloride 2.5 mg/500 mg tablets per day).

Patients with Inadequate Glycemic Control on Sulfonylurea Alone

In a 16-week, double-blind, active-controlled U.S. clinical trial, a total of 639 patients with type 2 diabetes not adequately controlled (mean baseline HbA1c 9.5%, mean baseline FPG 213 mg/dL) while being treated with at least one-half the maximum dose of a sulfonylurea (e.g., glyburide 10 mg, glipizide 20 mg) were randomized to receive glyburide (fixed dose, 20 mg), metformin (500 mg), glyburide and metformin hydrochloride 2.5 mg/500 mg, or glyburide and metformin hydrochloride 5 mg/500 mg. The doses of metformin and glyburide and metformin hydrochloride were titrated to a maximum of 4 tablets daily as needed to achieve FPG <140 mg/dL. Trial data at 16 weeks are summarized in Table 3.

Table 3: Glyburide and Metformin Hydrochloride in Patients with Inadequate Glycemic Control on Sulfonylurea Alone: Summary of Trial Data at 16 Weeks
 | Glyburide 5 mg Tablets | Metformin 500 mg Tablets | Glyburide and Metformin Hydrochloride 2.5 mg/500 mg Tablets | Glyburide and Metformin Hydrochloride 5 mg/500 mg Tablets
Mean Final Dose | 20 mg | 1840 mg | 8.8 mg/1760 mg | 17 mg/1740 mg
Hemoglobin A1c | N=158 | N=142 | N=154 | N=159
Baseline Mean (%) | 9.63 | 9.51 | 9.43 | 9.44
Final Mean | 9.61 | 9.82 | 7.92 | 7.91
Difference from Glyburide |  |  | -1.69a | -1.7a
Difference from Metformin |  |  | -1.9a | -1.91a
Fasting Plasma Glucose | N=163 | N=152 | N=160 | N=160
Baseline Mean (mg/dL) | 218.4 | 213.4 | 212.2 | 210.2
Final Mean | 221 | 233.8 | 169.6 | 161.1
Difference from Glyburide |  |  | -51.3a | -59.9a
Difference from Metformin |  |  | -64.2a | -72.7a
Body Weight Mean Change from Baseline | +0.43 kg | -2.76 kg | +0.75 kg | +0.47 kg
Final HbA1c Distribution (%) | N=158 | N=142 | N=154 | N=159
<7% | 2.5% | 2.8% | 24.7% | 22.6%
≥7% and <8% | 9.5% | 11.3% | 33.1% | 37.1%
≥8% | 88% | 85.9% | 42.2% | 40.3%
a p<0.001

After 16 weeks, there was no significant change in the mean HbA1c in patients randomized to glyburide or metformin therapy. Treatment with glyburide and metformin hydrochloride at doses up to 20 mg/2000 mg per day resulted in significant lowering of HbA1c, FPG, and PPG from baseline compared to glyburide or metformin alone.

Addition of Thiazolidinediones to Glyburide and Metformin Hydrochloride Therapy

In a 24-week, double-blind, multicenter U.S. clinical trial, patients with type 2 diabetes not adequately controlled on current oral antihyperglycemic therapy (either monotherapy or combination therapy) were first switched to open label glyburide and metformin hydrochloride 2.5 mg/500 mg tablets and titrated to a maximum daily dose of 10 mg/2000 mg. A total of 365 patients inadequately controlled (HbA1c >7% and ≤10%) after 10 to 12 weeks of a daily glyburide and metformin hydrochloride dose of at least 7.5 mg/1500 mg were randomized to receive add-on therapy with rosiglitazone 4 mg or placebo once daily. After 8 weeks, the rosiglitazone dose was increased to a maximum of 8 mg daily as needed to reach a target mean daily glucose of 126 mg/dL or HbA1c <7%. Trial data at 24 weeks or the last prior visit are summarized in Table 4.

Table 4: Effects of Adding Rosiglitazone or Placebo in Patients Treated with Glyburide and Metformin Hydrochloride in a 24-Week Trial
 | Placebo + Glyburide and Metformin Hydrochloride | Rosiglitazone + Glyburide and Metformin Hydrochloride
Mean Final Dose Glyburide and Metformin Hydrochloride Rosiglitazone | 10 mg/1992 mg 0 mg | 9.6 mg/1914 mg 7.4 mg
Hemoglobin A1c | N=178 | N=177
Baseline Mean (%) | 8.09 | 8.14
Final Mean | 8.21 | 7.23
Difference from Placeboa |  | -1.02b
Fasting Plasma Glucose | N=181 | N=176
Baseline Mean (mg/dL) | 173.1 | 178.4
Final Mean | 181.4 | 136.3
Difference from Placeboa |  | -48.5b
Body Weight Mean Change from Baseline | +0.03 kg | +3.03 kg
Final HbA1c Distribution (%) | N=178 | N=177
<7% | 13.5% | 42.4%
≥7% and <8% | 32% | 38.4%
≥8% | 54.5% | 19.2%
a Adjusted for the baseline mean difference
b p<0.001

For patients who did not achieve adequate glycemic control on glyburide and metformin hydrochloride, the addition of rosiglitazone, compared to placebo, resulted in significant lowering of HbA1c and FPG.

INDICATIONS AND USAGE

Glyburide and metformin hydrochloride tablets, USP are indicated as an adjunct to diet and exercise to improve glycemic control in adults with type 2 diabetes mellitus.

CONTRAINDICATIONS

Glyburide and metformin hydrochloride tablets are contraindicated in patients with:

1. Severe renal impairment (eGFR below 30 mL/min/1.73 m^2) (see WARNINGSand PRECAUTIONS).
2. Known hypersensitivity to metformin hydrochloride or glyburide.
3. Acute or chronic metabolic acidosis, including diabetic ketoacidosis, with or without coma. Diabetic ketoacidosis should be treated with insulin.
4. Concomitant administration of bosentan.

WARNINGS

Metformin Hydrochloride

WARNING: LACTIC ACIDOSIS

Post-marketing cases of metformin-associated lactic acidosis have resulted in death, hypothermia, hypotension, and resistant bradyarrhythmias. The onset of metformin-associated lactic acidosis is often subtle, accompanied only by nonspecific symptoms such as malaise, myalgias, respiratory distress, somnolence, and abdominal pain. Metformin-associated lactic acidosis was characterized by elevated blood lactate levels (>5 mmol/Liter), anion gap acidosis (without evidence of ketonuria or ketonemia), an increased lactate/pyruvate ratio; and metformin plasma levels generally >5 mcg/mL (see PRECAUTIONS).

Risk factors for metformin-associated lactic acidosis include renal impairment, concomitant use of certain drugs (e.g., carbonic anhydrase inhibitors such as topiramate), age 65 years old or greater, having a radiological study with contrast, surgery and other procedures, hypoxic states (e.g., acute congestive heart failure), excessive alcohol intake, and hepatic impairment.

Steps to reduce the risk of and manage metformin-associated lactic acidosis in these high risk groups are provided (see DOSAGE AND ADMINISTRATION, CONTRAINDICATIONS, and PRECAUTIONS).

If metformin-associated lactic acidosis is suspected, immediately discontinue glyburide and metformin hydrochloride and institute general supportive measures in a hospital setting. Prompt hemodialysis is recommended (see PRECAUTIONS).

SPECIAL WARNING ON INCREASED RISK OF CARDIOVASCULAR MORTALITY

The administration of oral hypoglycemic drugs has been reported to be associated with increased cardiovascular mortality as compared to treatment with diet alone or diet plus insulin. This warning is based on the study conducted by the University Group Diabetes Program (UGDP), a long-term prospective clinical trial designed to evaluate the effectiveness of glucose-lowering drugs in preventing or delaying vascular complications in patients with non-insulin-dependent diabetes. The study involved 823 patients who were randomly assigned to 1 of 4 treatment groups (Diabetes 19 (Suppl. 2):747-830, 1970).

UGDP reported that patients treated for 5 to 8 years with diet plus a fixed dose of tolbutamide (1.5 g per day) had a rate of cardiovascular mortality approximately 2½ times that of patients treated with diet alone. A significant increase in total mortality was not observed, but the use of tolbutamide was discontinued based on the increase in cardiovascular mortality, thus limiting the opportunity for the study to show an increase in overall mortality. Despite controversy regarding the interpretation of these results, the findings of the UGDP study provide an adequate basis for this warning. The patient should be informed of the potential risks and benefits of glyburide and of alternative modes of therapy.

Although only 1 drug in the sulfonylurea class (tolbutamide) was included in this study, it is prudent from a safety standpoint to consider that this warning may also apply to other hypoglycemic drugs in this class, in view of their close similarities in mode of action and chemical structure.

PRECAUTIONS

GENERAL PRECAUTIONS

Glyburide and Metformin Hydrochloride

Lactic Acidosis

There have been post-marketing cases of metformin-associated lactic acidosis, including fatal cases. These cases had a subtle onset and were accompanied by nonspecific symptoms such as malaise, myalgias, abdominal pain, respiratory distress, or increased somnolence; however, hypotension and resistant bradyarrhythmias have occurred with severe acidosis. Metformin-associated lactic acidosis was characterized by elevated blood lactate concentrations (>5 mmol/L), anion gap acidosis (without evidence of ketonuria or ketonemia), and an increased lactate:pyruvate ratio; metformin plasma levels were generally >5 mcg/mL. Metformin decreases liver uptake of lactate increasing lactate blood levels which may increase the risk of lactic acidosis, especially in patients at risk.

If metformin-associated lactic acidosis is suspected, general supportive measures should be instituted promptly in a hospital setting, along with immediate discontinuation of glyburide and metformin hydrochloride. In glyburide and metformin hydrochloride treated patients with a diagnosis or strong suspicion of lactic acidosis, prompt hemodialysis is recommended to correct the acidosis and remove accumulated metformin (metformin hydrochloride is dialyzable with a clearance of up to 170 mL/min under good hemodynamic conditions). Hemodialysis has often resulted in reversal of symptoms and recovery.

Educate patients and their families about the symptoms of lactic acidosis and if these symptoms occur instruct them to discontinue glyburide and metformin hydrochloride and report these symptoms to their healthcare provider.

For each of the known and possible risk factors for metformin-associated lactic acidosis, recommendations to reduce the risk of and manage metformin-associated lactic acidosis are provided below:

• Renal Impairment - The postmarketing metformin-associated lactic acidosis cases primarily

occurred in patients with significant renal impairment.

The risk of metformin accumulation and metformin-associated lactic acidosis increases with the severity of renal impairment because metformin is substantially excreted by the kidney. Clinical recommendations based upon the patient’s renal function include (see DOSAGE AND ADMINISTRATION, CLINICAL PHARMACOLOGY):

- Before initiating glyburide and metformin hydrochloride, obtain an estimated glomerular filtration rate (eGFR).
- Glyburide and metformin hydrochloride is contraindicated in patients with an eGFR less than 30 mL/min/1.73 m^2 (see CONTRAINDICATIONS).
- Initiation of glyburide and metformin hydrochloride is not recommended in patients with eGFR between 30 to 45 mL/min/1.73 m^2 .
- Obtain an eGFR at least annually in all patient taking glyburide and metformin hydrochloride. In patients at risk for the development of renal impairment (e.g., the elderly), renal function should be assessed more frequently.

- In patients taking glyburide and metformin hydrochloride whose eGFR falls below 45 mL/min/1.73 m^2, assess the benefit and risk of continuing therapy.

- Drug interactions - The concomitant use of glyburide and metformin hydrochloride with specific drugs may increase the risk of metformin-associated lactic acidosis: those that impair renal function, result in significant hemodynamic change, interfere with acid-base balance, or increase metformin accumulation. Consider more frequent monitoring of patients.

- Age 65 or Greater- The risk of metformin-associated lactic acidosis increases with the patient’s age because elderly patients have a greater likelihood of having hepatic, renal, or cardiac impairment than younger patients. Assess renal function more frequently in elderly patients.

- Radiologic studies with contrast - Administration of intravascular iodinated contrast agents in metformin-treated patients has led to an acute decrease in renal function and the occurrence of lactic acidosis. Stop glyburide and metformin hydrochloride at the time of, or prior to, an iodinated contrast imaging procedure in patients with an eGFR between 30 and 60 mL/min/1.73 m^2; in patients with a history of hepatic impairment, alcoholism or heart failure, or in patients who will be administered intra-arterial iodinated contrast. Reevaluate eGFR 48 hours after the imaging procedure, and restart glyburide and metformin hydrochloride if renal function is stable.

- Surgery and other procedures - Withholding of food and fluids during surgical or other procedures may increase the risk for volume depletion, hypotension, and renal impairment. Glyburide and metformin hydrochloride should be temporarily discontinued while patients have restricted food and fluid intake.

- Hypoxic states - Several of the postmarketing cases of metformin-associated lactic acidosis occurred in the setting of acute congestive heart failure (particularly when accompanied by hypoperfusion and hypoxemia). Cardiovascular collapse (shock), acute myocardial infarction, sepsis, and other conditions associated with hypoxemia have been associated with lactic acidosis and may cause prerenal azotemia. When such an event occurs, discontinue glyburide and metformin hydrochloride.

- Excessive Alcohol intake - Alcohol is known to potentiate the effect of metformin on lactate metabolism. Patients, therefore, should be warned against excessive alcohol intake, acute or chronic, while receiving glyburide and metformin hydrochloride.

- Hepatic impairment - Patients with hepatic impairment have developed cases of metformin-associated lactic acidosis. This may be due to impaired lactate clearance resulting in higher lactate blood levels. Therefore, avoid use of glyburide and metformin hydrochloride in patients with clinical or laboratory evidence of hepatic disease.

Hypoglycemia

Glyburide and metformin hydrochloride is capable of producing hypoglycemia or hypoglycemic symptoms, therefore, proper patient selection, dosing, and instructions are important to avoid potential hypoglycemic episodes. The risk of hypoglycemia is increased when caloric intake is deficient, when strenuous exercise is not compensated by caloric supplementation, or during concomitant use with other glucose-lowering agents or ethanol. Renal or hepatic insufficiency may cause elevated drug levels of both glyburide and metformin hydrochloride, and the hepatic insufficiency may also diminish gluconeogenic capacity, both of which increase the risk of hypoglycemic reactions. Elderly, debilitated, or malnourished patients and those with adrenal or pituitary insufficiency or alcohol intoxication are particularly susceptible to hypoglycemic effects. Hypoglycemia may be difficult to recognize in the elderly and people who are taking beta-adrenergic blocking drugs.

Glyburide

Hemolytic anemia
Treatment of patients with glucose-6-phosphate dehydrogenase (G6PD) deficiency with sulfonylurea agents can lead to hemolytic anemia. Because glyburide and metformin hydrochloride belongs to the class of sulfonylurea agents, caution should be used in patients with G6PD deficiency and a non-sulfonylurea alternative should be considered. In postmarketing reports, hemolytic anemia has also been reported in patients who did not have known G6PD deficiency.

Metformin Hydrochloride

Vitamin B12 levels

In controlled clinical trials with metformin of 29 weeks duration, a decrease to subnormal levels of previously normal serum vitamin B12, without clinical manifestations, was observed in approximately 7% of patients. Such decrease, possibly due to interference with B12 absorption from the B12-intrinsic factor complex is, however, very rarely associated with anemia and appears to be rapidly reversible with discontinuation of metformin or vitamin B12 supplementation. Measurement of hematologic parameters on an annual basis is advised in patients on metformin and any apparent abnormalities should be appropriately investigated and managed (see PRECAUTIONS: Laboratory Tests).

Certain individuals (those with inadequate vitamin B12 or calcium intake or absorption) appear to be predisposed to developing subnormal vitamin B12 levels. In these patients, routine serum vitamin B12 measurements at 2- to 3-year intervals may be useful.

Macrovascular Outcomes

There have been no clinical studies establishing conclusive evidence of macrovascular risk reduction with glyburide and metformin hydrochloride or any other antidiabetic drug.

Addition of Thiazolidinediones to Glyburide and Metformin Hydrochloride Therapy

Hypoglycemia

Patients receiving glyburide and metformin hydrochloride in combination with a thiazolidinedione may be at risk for hypoglycemia.

Weight gain

Weight gain was seen with the addition of rosiglitazone to glyburide and metformin hydrochloride, similar to that reported for thiazolidinedione therapy alone.

Hepatic effects

When a thiazolidinedione is used in combination with glyburide and metformin hydrochloride, periodic monitoring of liver function tests should be performed in compliance with the labeled recommendations for the thiazolidinedione.

Information for Patients

Glyburide and Metformin Hydrochloride

Patients should be informed of the potential risks and benefits of glyburide and metformin hydrochloride and alternative modes of therapy. They should also be informed about the importance of adherence to dietary instructions; a regular exercise program; and regular testing of blood glucose, glycosylated hemoglobin, renal function, and hematologic parameters.

The risks of lactic acidosis associated with metformin therapy, its symptoms, and conditions that predispose to its development, as noted in the WARNINGS and PRECAUTIONS sections, should be explained to patients. Patients should be advised to discontinue glyburide and metformin hydrochloride immediately and promptly notify their health practitioner if unexplained hyperventilation, myalgia, malaise, unusual somnolence, or other nonspecific symptoms occur. Once a patient is stabilized on any dose level of glyburide and metformin hydrochloride, gastrointestinal symptoms, which are common during initiation of metformin therapy, are unlikely to be drug related. Later occurrence of gastrointestinal symptoms could be due to lactic acidosis or other serious disease.

The risks of hypoglycemia, its symptoms and treatment, and conditions that predispose to its development should be explained to patients and responsible family members.

Patients should be counseled against excessive alcohol intake, either acute or chronic, while receiving glyburide and metformin hydrochloride. (See Patient Information printed below.)

Laboratory Tests

Periodic fasting blood glucose (FBG) and HbA1c measurements should be performed to monitor therapeutic response.

Initial and periodic monitoring of hematologic parameters (e.g., hemoglobin/hematocrit and red blood cell indices) and renal function (serum creatinine) should be performed, at least on an annual basis. While megaloblastic anemia has rarely been seen with metformin therapy, if this is suspected, vitamin B12 deficiency should be excluded.

Instruct patients to inform their doctor that they are taking glyburide and metformin hydrochloride prior to any surgical or radiological procedure, as temporary discontinuation of glyburide and metformin hydrochloride may be required until renal function has been confirmed to be normal (see PRECAUTIONS).

Drug Interactions

Glyburide and Metformin Hydrochloride

Certain drugs tend to produce hyperglycemia and may lead to loss of blood glucose control. These drugs include thiazides and other diuretics, corticosteroids, phenothiazines, thyroid products, estrogens, oral contraceptives, phenytoin, nicotinic acid, sympathomimetics, calcium channel blocking drugs, and isoniazid. When such drugs are administered to a patient receiving glyburide and metformin hydrochloride, the patient should be closely observed for loss of blood glucose control. When such drugs are withdrawn from a patient receiving glyburide and metformin hydrochloride, the patient should be observed closely for hypoglycemia. Metformin is negligibly bound to plasma proteins and is, therefore, less likely to interact with highly protein-bound drugs such as salicylates, sulfonamides, chloramphenicol, and probenecid as compared to sulfonylureas, which are extensively bound to serum proteins.

Glyburide

The hypoglycemic action of sulfonylureas may be potentiated by certain drugs, including nonsteroidal anti-inflammatory agents and other drugs that are highly protein bound, salicylates, sulfonamides, chloramphenicol, probenecid, coumarins, monoamine oxidase inhibitors, and beta-adrenergic blocking agents. When such drugs are administered to a patient receiving glyburide and metformin hydrochloride, the patient should be observed closely for hypoglycemia. When such drugs are withdrawn from a patient receiving glyburide and metformin hydrochloride, the patient should be observed closely for loss of blood glucose control.
An increased risk of liver enzyme elevations was observed in patients receiving glyburide concomitantly with bosentan. Therefore concomitant administration of glyburide and metformin hydrochloride and bosentan is contraindicated.
A possible interaction between glyburide and ciprofloxacin, a fluoroquinolone antibiotic, has been reported, resulting in a potentiation of the hypoglycemic action of glyburide. The mechanism for this interaction is not known.
A potential interaction between oral miconazole and oral hypoglycemic agents leading to severe hypoglycemia has been reported. Whether this interaction also occurs with the intravenous, topical, or vaginal preparations of miconazole is not known.
Colesevelam: Concomitant administration of colesevelam and glyburide resulted in reductions in glyburide AUC and Cmax of 32% and 47%, respectively. The reductions in glyburide AUC and Cmax were 20% and 15%, respectively, when administered 1 hour before, and not significantly changed (−7% and 4%, respectively) when administered 4 hours before colesevelam.

Metformin Hydrochloride

Furosemide

A single-dose, metformin-furosemide drug interaction study in healthy subjects demonstrated that pharmacokinetic parameters of both compounds were affected by coadministration. Furosemide increased the metformin plasma and blood Cmax by 22% and blood AUC by 15%, without any significant change in metformin renal clearance. When administered with metformin, the Cmax and AUC of furosemide were 31% and 12% smaller, respectively, than when administered alone, and the terminal half-life was decreased by 32%, without any significant change in furosemide renal clearance. No information is available about the interaction of metformin and furosemide when coadministered chronically.

Nifedipine

A single-dose, metformin-nifedipine drug interaction study in normal healthy volunteers demonstrated that coadministration of nifedipine increased plasma metformin Cmax and AUC by 20% and 9%, respectively, and increased the amount excreted in the urine. Tmax and half-life were unaffected. Nifedipine appears to enhance the absorption of metformin. Metformin had minimal effects on nifedipine.

Drugs that reduce metformin clearance

Concomitant use of drugs that interfere with common renal tubular transport systems involved in the renal elimination of metformin (e.g., organic cationic transport-2 [OCT2] / multidrug and toxin extrusion [MATE] inhibitors such as ranolazine, vandetanib, dolutegravir, and cimetidine) could increase systemic exposure to metformin and may increase the accumulation of metformin and the risk for lactic acidosis. Consider the benefits and risks of concomitant use. Such interaction between metformin and oral cimetidine has been observed in normal healthy volunteers in both single- and multiple-dose, metformin-cimetidine drug interaction studies, with a 60% increase in peak metformin plasma and whole blood concentrations and a 40% increase in plasma and whole blood metformin AUC. There was no change in elimination half-life in the single-dose study. Metformin had no effect on cimetidine pharmacokinetics.

In healthy volunteers, the pharmacokinetics of metformin and propranolol, and metformin and ibuprofen were not affected when coadministered in single-dose interaction studies.

Metformin is negligibly bound to plasma proteins and is, therefore, less likely to interact with highly protein-bound drugs such as salicylates, sulfonamides, chloramphenicol, and probenecid, as compared to the sulfonylureas, which are extensively bound to serum proteins.

Carbonic Anhydrase Inhibitors

Topiramate or other carbonic anhydrase inhibitors (e.g., zonisamide, acetazolamide or dichlorphenamide) frequently causes a decrease in serum bicarbonate and induce non-anion gap, hyperchloremic metabolic acidosis. Concomitant use of these drugs with glyburide and metformin hydrochloride may increase the risk for lactic acidosis. Consider more frequent monitoring of these patients.

Alcohol

Alcohol is known to potentiate the effects of metformin on lactate metabolism. Warn patients against excessive alcohol intake while receiving glyburide and metformin hydrochloride.

Carcinogenesis, Mutagenesis, Impairment of Fertility

No animal studies have been conducted with the combined products in glyburide and metformin hydrochloride. The following data are based on findings in studies performed with the individual products.

Glyburide

Studies in rats with glyburide alone at doses up to 300 mg/kg/day (approximately 145 times the maximum recommended human daily [MRHD] dose of 20 mg for the glyburide component of glyburide and metformin hydrochloride based on body surface area comparisons) for 18 months revealed no carcinogenic effects. In a 2-year oncogenicity study of glyburide in mice, there was no evidence of treatment-related tumors.
There was no evidence of mutagenic potential of glyburide alone in the following in vitro tests: Salmonella microsome test (Ames test) and in the DNA damage/alkaline elution assay.

Metformin Hydrochloride

Long-term carcinogenicity studies were performed with metformin alone in rats (dosing duration of 104 weeks) and mice (dosing duration of 91 weeks) at doses up to and including 900 mg/kg/day and 1500 mg/kg/day, respectively. These doses are both approximately 4 times the MRHD dose of 2000 mg of the metformin component of glyburide and metformin hydrochloride based on body surface area comparisons. No evidence of carcinogenicity with metformin alone was found in either male or female mice. Similarly, there was no tumorigenic potential observed with metformin alone in male rats. There was, however, an increased incidence of benign stromal uterine polyps in female rats treated with 900 mg/kg/day of metformin alone.
There was no evidence of a mutagenic potential of metformin alone in the following in vitro tests: Ames test (S. typhimurium), gene mutation test (mouse lymphoma cells), or chromosomal aberrations test (human lymphocytes). Results in the in vivo mouse micronucleus test were also negative.
Fertility of male or female rats was unaffected by metformin alone when administered at doses as high as 600 mg/kg/day, which is approximately 3 times the MRHD dose of the metformin component of glyburide and metformin hydrochloride based on body surface area comparisons.

Pregnancy

Teratogenic Effects

Pregnancy Category B
Recent information strongly suggests that abnormal blood glucose levels during pregnancy are associated with a higher incidence of congenital abnormalities. Most experts recommend that insulin be used during pregnancy to maintain blood glucose as close to normal as possible. Because animal reproduction studies are not always predictive of human response, glyburide and metformin hydrochloride should not be used during pregnancy unless clearly needed. (See below.)
There are no adequate and well-controlled studies in pregnant women with glyburide and metformin hydrochloride or its individual components. No animal studies have been conducted with the combined products in glyburide and metformin hydrochloride. The following data are based on findings in studies performed with the individual products.
Glyburide
Reproduction studies were performed in rats and rabbits at doses up to 500 times the MRHD dose of 20 mg of the glyburide component of glyburide and metformin hydrochloride based on body surface area comparisons and revealed no evidence of impaired fertility or harm to the fetus due to glyburide.
Metformin Hydrochloride
Metformin alone was not teratogenic in rats or rabbits at doses up to 600 mg/kg/day. This represents an exposure of about 2 and 6 times the MRHD dose of 2000 mg of the metformin component of glyburide and metformin hydrochloride based on body surface area comparisons for rats and rabbits, respectively. Determination of fetal concentrations demonstrated a partial placental barrier to metformin.

Nonteratogenic Effects

Prolonged severe hypoglycemia (4 to 10 days) has been reported in neonates born to mothers who were receiving a sulfonylurea drug at the time of delivery. This has been reported more frequently with the use of agents with prolonged half-lives. It is not recommended that glyburide and metformin hydrochloride be used during pregnancy. However, if it is used, glyburide and metformin hydrochloride should be discontinued at least 2 weeks before the expected delivery date. (See Pregnancy: Teratogenic Effects: Pregnancy Category B.)

Nursing Mothers

Although it is not known whether glyburide is excreted in human milk, some sulfonylurea drugs are known to be excreted in human milk. Studies in lactating rats show that metformin is excreted into milk and reaches levels comparable to those in plasma. Similar studies have not been conducted in nursing mothers. Because the potential for hypoglycemia in nursing infants may exist, a decision should be made whether to discontinue nursing or to discontinue glyburide and metformin hydrochloride, taking into account the importance of the drug to the mother. If glyburide and metformin hydrochloride is discontinued, and if diet alone is inadequate for controlling blood glucose, insulin therapy should be considered.

Pediatric Use

The safety and efficacy of glyburide and metformin hydrochloride were evaluated in an active-controlled, double-blind, 26-week randomized trial involving a total of 167 pediatric patients (ranging from 9 to 16 years of age) with type 2 diabetes. Glyburide and metformin hydrochloride was not shown statistically to be superior to either metformin or glyburide with respect to reducing HbA1c from baseline (see Table 5). No unexpected safety findings were associated with glyburide and metformin hydrochloride in this trial.

Table 5: HbA1c (Percent) Change From Baseline at 26 Weeks: Pediatric Study
 | Glyburide 2.5 mg Tablets | Metformin 500 mg Tablets | Glyburide and Metformin Hydrochloride 1.25 mg/250 mg Tablets
Mean Final Dose | 6.5 mg | 1500 mg | 3.1 mg/623 mg
Hemoglobin A1c | N=49 | N=54 | N=57
Baseline Mean (%) | 7.7 | 7.99 | 7.85
Mean Change from Baseline | -0.96 | -0.48 | -0.8
Difference from Metformin Difference from Glyburide |  |  | -0.32 +0.16

Geriatric Use

Of the 642 patients who received glyburide and metformin hydrochloride in double-blind clinical studies, 23.8% were 65 and older while 2.8% were 75 and older. Of the 1302 patients who received glyburide and metformin hydrochloride in open-label clinical studies, 20.7% were 65 and older while 2.5% were 75 and older. No overall differences in effectiveness or safety were observed between these patients and younger patients, and other reported clinical experience has not identified differences in response between the elderly and younger patients, but greater sensitivity of some older individuals cannot be ruled out.

In general, dose selection for an elderly patient should be cautious, usually starting at the low end of the dosing range, reflecting the greater frequency of decreased hepatic, renal, or cardiac function, and of concomitant disease or other drug therapy and the higher risk of lactic acidosis. Assess renal function more frequently in elderly patients (see also WARNINGS, PRECAUTIONS, and DOSAGE AND ADMINISTRATION).

ADVERSE REACTIONS

Glyburide and Metformin Hydrochloride

In double-blind clinical trials involving glyburide and metformin hydrochloride as initial therapy or as second-line therapy, a total of 642 patients received glyburide and metformin hydrochloride, 312 received metformin therapy, 324 received glyburide therapy, and 161 received placebo. The percent of patients reporting events and types of adverse events reported in clinical trials of glyburide and metformin hydrochloride (all strengths) as initial therapy and second-line therapy are listed in Table 6.

Table 6: Most Common Clinical Adverse Events (>5%) in Double-Blind Clinical Studies of Glyburide and Metformin Hydrochloride Used as Initial or Second-Line Therapy
Adverse Event | Number (%) of Patients
Adverse Event | Placebo N=161 | Glyburide N=324 | Metformin N=312 | Glyburide and Metformin Hydrochloride N=642
Upper respiratory infection | 22 (13.7) | 57 (17.6) | 51 (16.3) | 111 (17.3)
Diarrhea | 9 (5.6) | 20 (6.2) | 64 (20.5) | 109 (17)
Headache | 17 (10.6) | 37 (11.4) | 29 (9.3) | 57 (8.9)
Nausea/vomiting | 10 (6.2) | 17 (5.2) | 38 (12.2) | 49 (7.6)
Abdominal pain | 6 (3.7) | 10 (3.1) | 25 (8) | 44 (6.9)
Dizziness | 7 (4.3) | 18 (5.6) | 12 (3.8) | 35 (5.5)

In a controlled clinical trial of rosiglitazone versus placebo in patients treated with glyburide and metformin hydrochloride (n=365), 181 patients received glyburide and metformin hydrochloride with rosiglitazone and 184 received glyburide and metformin hydrochloride with placebo.
Edema was reported in 7.7% (14/181) of patients treated with rosiglitazone compared to 2.2% (4/184) of patients treated with placebo. A mean weight gain of 3 kg was observed in rosiglitazone-treated patients.
Disulfiram-like reactions have very rarely been reported in patients treated with glyburide tablets.

Hypoglycemia

In controlled clinical trials of glyburide and metformin hydrochloride there were no hypoglycemic episodes requiring medical intervention and/or pharmacologic therapy; all events were managed by the patients. The incidence of reported symptoms of hypoglycemia (such as dizziness, shakiness, sweating, and hunger), in the initial therapy trial of glyburide and metformin hydrochloride are summarized in Table 7. The frequency of hypoglycemic symptoms in patients treated with glyburide and metformin hydrochloride 1.25 mg/250 mg was highest in patients with a baseline HbA1c <7%, lower in those with a baseline HbA1c of between 7% and 8%, and was comparable to placebo and metformin in those with a baseline HbA1c >8%. For patients with a baseline HbA1c between 8% and 11% treated with glyburide and metformin hydrochloride 2.5 mg/500 mg as initial therapy, the frequency of hypoglycemic symptoms was 30% to 35%. As second-line therapy in patients inadequately controlled on sulfonylurea alone, approximately 6.8% of all patients treated with glyburide and metformin hydrochloride experienced hypoglycemic symptoms. When rosiglitazone was added to glyburide and metformin hydrochloride therapy, 22% of patients reported 1 or more fingerstick glucose measurements ≤50 mg/dL compared to 3.3% of placebo-treated patients. All hypoglycemic events were managed by the patients and only 1 patient discontinued for hypoglycemia. (See PRECAUTIONS: General: Addition of Thiazolidinediones to Glyburide and Metformin Hydrochloride Therapy.)

Gastrointestinal Reactions

The incidence of gastrointestinal (GI) side effects (diarrhea, nausea/vomiting, and abdominal pain) in the initial therapy trial are summarized in Table 7. Across all glyburide and metformin hydrochloride trials, GI symptoms were the most common adverse events with glyburide and metformin hydrochloride and were more frequent at higher dose levels. In controlled trials, <2% of patients discontinued glyburide and metformin hydrochloride therapy due to GI adverse events.

Table 7: Treatment Emergent Symptoms of Hypoglycemia or Gastrointestinal Adverse Events in a Placebo- and Active-Controlled Trial of Glyburide and Metformin Hydrochloride as Initial Therapy
Variable | Placebo N=161 | Glyburide Tablets N=160 | Metformin Tablets N=159 | Glyburide and Metformin Hydrochloride 1.25 mg/250 mg Tablets N=158 | Glyburide and Metformin Hydrochloride 2.5 mg/500 mg Tablets N=162
Mean Final Dose | 0 mg | 5.3 mg | 1317 mg | 2.78 mg/557 mg | 4.1 mg/824 mg
Number (%) of patients with symptoms of hypoglycemia | 5 (3.1) | 34 (21.3) | 5 (3.1) | 18 (11.4) | 61 (37.7)
Number (%) of patients with gastrointestinal adverse events | 39 (24.2) | 38 (23.8) | 69 (43.3) | 50 (31.6) | 62 (38.3)

Metformin Hydrochloride

Cholestatic, hepatocellular, and mixed hepatocellular liver injury have been reported with postmarketing use of metformin.

Glyburide

Gastrointestinal Reactions

Cholestatic jaundice and hepatitis may occur rarely which may progress to liver failure; the drug should be discontinued if this occurs. Liver function abnormalities, including isolated transaminase elevations, have been reported.

Dermatologic Reactions

Allergic skin reactions, e.g., pruritus, erythema, urticaria, and morbilliform or maculopapular eruptions, occur in 1.5% of glyburide-treated patients. These may be transient and may disappear despite continued use; if skin reactions persist, the drug should be discontinued.

Postmarketing Adverse Reactions

The following adverse reactions have been identified during post-approval use. Because these reactions are reported voluntarily from a population of uncertain size, it is generally not possible to reliably estimate their frequency or establish a causal relationship to drug exposure.

Allergic: Angioedema, arthralgia, myalgia, and vasculitis have been reported.

Dermatologic: Porphyria cutanea tarda and photosensitivity reactions have been reported with sulfonylureas.

Hematologic: Leukopenia, agranulocytosis, thrombocytopenia, which occasionally may present as purpura, hemolytic anemia, aplastic anemia, and pancytopenia, have been reported with sulfonylureas.

Metabolic: Hepatic porphyria reactions have been reported with sulfonylureas; however, these have not been reported with glyburide. Disulfiram-like reactions have been reported very rarely with glyburide. Cases of hyponatremia have been reported with glyburide and all other sulfonylureas, most often in patients who are on other medications or have medical conditions known to cause hyponatremia or increase release of antidiuretic hormone.

Other Reactions: Changes in accommodation and/or blurred vision have been reported with glyburide and other sulfonylureas. These are thought to be related to fluctuation in glucose levels.

OVERDOSAGE

Glyburide

Overdosage of sulfonylureas, including glyburide tablets, can produce hypoglycemia. Mild hypoglycemic symptoms, without loss of consciousness or neurological findings, should be treated aggressively with oral glucose and adjustments in drug dosage and/or meal patterns. Close monitoring should continue until the physician is assured that the patient is out of danger. Severe hypoglycemic reactions with coma, seizure, or other neurological impairment occur infrequently, but constitute medical emergencies requiring immediate hospitalization. If hypoglycemic coma is diagnosed or suspected, the patient should be given a rapid intravenous injection of concentrated (50%) glucose solution. This should be followed by a continuous infusion of a more dilute (10%) glucose solution at a rate that will maintain the blood glucose at a level above 100 mg/dL. Patients should be closely monitored for a minimum of 24 to 48 hours, since hypoglycemia may recur after apparent clinical recovery.

Metformin Hydrochloride

Overdose of metformin hydrochloride has occurred, including ingestion of amounts >50 g. Hypoglycemia was reported in approximately 10% of cases, but no causal association with metformin hydrochloride has been established. Lactic acidosis has been reported in approximately 32% of metformin overdose cases (see WARNINGS). Metformin is dialyzable with a clearance of up to 170 mL/min under good hemodynamic conditions. Therefore, hemodialysis may be useful for removal of accumulated drug from patients in whom metformin overdosage is suspected.

DOSAGE AND ADMINISTRATION

General Considerations

Dosage of glyburide and metformin hydrochloride tablets must be individualized on the basis of both effectiveness and tolerance while not exceeding the maximum recommended daily dose of 20 mg glyburide/2000 mg metformin. Glyburide and metformin hydrochloride tablets should be given with meals and should be initiated at a low dose, with gradual dose escalation as described below, in order to avoid hypoglycemia (largely due to glyburide), reduce GI side effects (largely due to metformin), and permit determination of the minimum effective dose for adequate control of blood glucose for the individual patient.
With initial treatment and during dose titration, appropriate blood glucose monitoring should be used to determine the therapeutic response to glyburide and metformin hydrochloride tablets and to identify the minimum effective dose for the patient. Thereafter, HbA1c should be measured at intervals of approximately 3 months to assess the effectiveness of therapy. The therapeutic goal in all patients with type 2 diabetes is to decrease FPG, PPG, and HbA1c to normal or as near normal as possible. Ideally, the response to therapy should be evaluated using HbA1c (glycosylated hemoglobin), which is a better indicator of long-term glycemic control than FPG alone.
No studies have been performed specifically examining the safety and efficacy of switching to glyburide and metformin hydrochloride tablets therapy in patients taking concomitant glyburide (or other sulfonylurea) plus metformin. Changes in glycemic control may occur in such patients, with either hyperglycemia or hypoglycemia possible. Any change in therapy of type 2 diabetes should be undertaken with care and appropriate monitoring.

In Patients with Inadequate Glycemic Control on Diet and Exercise

Recommended starting dose: 1.25 mg glyburide and 250 mg metformin hydrochloride once or twice daily with meals.

For patients with type 2 diabetes whose hyperglycemia cannot be satisfactorily managed with diet and exercise alone, the recommended starting dose is 1.25 mg glyburide and 250 mg metformin hydrochloride once a day with a meal. As initial therapy in patients with baseline HbA1c >9% or an FPG >200 mg/dL, a starting dose of 1.25 mg glyburide and 250 mg metformin hydrochloride twice daily with the morning and evening meals may be used. Dosage increases should be made in increments of 1.25 mg glyburide and 250 mg metformin hydrochloride per day every 2 weeks up to the minimum effective dose necessary to achieve adequate control of blood glucose. In clinical trials of glyburide and metformin hydrochloride tablets as initial therapy, there was no experience with total daily doses >10 mg/2000 mg per day. Glyburide and metformin hydrochloride tablets 5 mg/500 mg should not be used as initial therapy due to an increased risk of hypoglycemia.

Glyburide and Metformin Hydrochloride Tablets Use in Patients with Inadequate Glycemic Control on a Sulfonylurea and/or Metformin

Recommended starting dose: 2.5 mg/500 mg or 5 mg/500 mg twice daily with meals.
For patients not adequately controlled on either glyburide (or another sulfonylurea) or metformin alone, the recommended starting dose of glyburide and metformin hydrochloride tablets is 2.5 mg/500 mg or 5 mg/500 mg twice daily with the morning and evening meals. In order to avoid hypoglycemia, the starting dose of glyburide and metformin hydrochloride tablets should not exceed the daily doses of glyburide or metformin already being taken. The daily dose should be titrated in increments of no more than 5 mg/500 mg up to the minimum effective dose to achieve adequate control of blood glucose or to a maximum dose of 20 mg/2000 mg per day.
For patients previously treated with combination therapy of glyburide (or another sulfonylurea) plus metformin, if switched to glyburide and metformin hydrochloride tablets, the starting dose should not exceed the daily dose of glyburide (or equivalent dose of another sulfonylurea) and metformin already being taken. Patients should be monitored closely for signs and symptoms of hypoglycemia following such a switch and the dose of glyburide and metformin hydrochloride tablets should be titrated as described above to achieve adequate control of blood glucose.

Addition of Thiazolidinediones to Glyburide and Metformin Hydrochloride Tablets Therapy

For patients not adequately controlled on glyburide and metformin hydrochloride tablets, a thiazolidinedione can be added to glyburide and metformin hydrochloride tablets therapy. When a thiazolidinedione is added to glyburide and metformin hydrochloride tablets therapy, the current dose of glyburide and metformin hydrochloride tablets can be continued and the thiazolidinedione initiated at its recommended starting dose. For patients needing additional glycemic control, the dose of the thiazolidinedione can be increased based on its recommended titration schedule. The increased glycemic control attainable with glyburide and metformin hydrochloride tablets plus a thiazolidinedione may increase the potential for hypoglycemia at any time of day. In patients who develop hypoglycemia when receiving glyburide and metformin hydrochloride tablets and a thiazolidinedione, consideration should be given to reducing the dose of the glyburide component of glyburide and metformin hydrochloride tablets. As clinically warranted, adjustment of the dosages of the other components of the antidiabetic regimen should also be considered.

Patients Receiving Colesevelam

When colesevelam is coadministered with glyburide, maximum plasma concentration and total exposure to glyburide is reduced. Therefore, glyburide and metformin hydrochloride tablets should be administered at least 4 hours prior to colesevelam.

Recommendations for Use in Renal Impairment

Assess renal function prior to initiation of glyburide and metformin hydrochloride tablets and periodically thereafter.

Glyburide and metformin hydrochloride tablets are contraindicated in patients with an estimated glomerular filtration rate (eGFR) below 30 mL/minute/1.73 m^2 .

Initiation of glyburide and metformin hydrochloride tablets in patients with an eGFR between 30 to 45 mL/minute/1.73 m^2 is not recommended.

In patients taking glyburide and metformin hydrochloride tablets whose eGFR later falls below 45 mL/min/1.73 m^2, assess the benefit risk of continuing therapy.

Discontinue glyburide and metformin hydrochloride tablets if the patient’s eGFR later falls below 30 mL/minute/1.73 m^2 (see WARNINGS and PRECAUTIONS).

Discontinuation for Iodinated Contrast Imaging Procedures

Discontinue glyburide and metformin hydrochloride tablets at the time of, or prior to, an iodinated contrast imaging procedure in patients with an eGFR between 30 and 60 mL/min/1.73 m^2; in patients with a history of liver disease, alcoholism or heart failure; or in patients who will be administered intra-arterial iodinated contrast. Re-evaluate eGFR 48 hours after the imaging procedure; restart glyburide and metformin hydrochloride tablets if renal function is stable.

Specific Patient Populations

Glyburide and metformin hydrochloride tablets are not recommended for use during pregnancy. The initial and maintenance dosing of glyburide and metformin hydrochloride tablets should be conservative in patients with advanced age, due to the potential for decreased renal function in this population. Any dosage adjustment requires a careful assessment of renal function.

HOW SUPPLIED

Glyburide and Metformin Hydrochloride Tablets USP, 5 mg/500 mg: Yellow, capsule shaped, biconvex, film-coated tablet with A debossed on one side and 48 on the other side.
NDC 68071-4718-3 BOTTLES OF 30
Store at 20° to 25°C (68° to 77°F); excursions permitted to 15° to 30°C (59° to 86°F) [see USP Controlled Room Temperature].
Dispense in light-resistant containers.

PATIENT INFORMATION ABOUT

Glyburide and Metformin Hydrochloride Tablets, USP
(glye' bure ide and met for' min hye'' droe klor' ide)
Rx only

WARNING:

A small number of people who have taken metformin hydrochloride have developed a serious condition called lactic acidosis. Properly functioning kidneys are needed to help prevent lactic acidosis. Most people with kidney problems should not take glyburide and metformin hydrochloride. (See Question Nos. 9-13.)

Q1. Why do I need to take glyburide and metformin hydrochloride?

Your doctor has prescribed glyburide and metformin hydrochloride to treat your type 2 diabetes. This is also known as non-insulin-dependent diabetes mellitus.

Q2. What is type 2 diabetes?

People with diabetes are not able to make enough insulin and/or respond normally to the insulin their body does make. When this happens, sugar (glucose) builds up in the blood. This can lead to serious medical problems, including kidney damage, amputations, and blindness. Diabetes is also closely linked to heart disease. The main goal of treating diabetes is to lower your blood sugar to a normal level.

Q3. Why is it important to control type 2 diabetes?

The main goal of treating diabetes is to lower your blood sugar to a normal level. Studies have shown that good control of blood sugar may prevent or delay complications, such as heart disease, kidney disease, or blindness.

Q4. How is type 2 diabetes usually controlled?

High blood sugar can be lowered by diet and exercise, a number of oral medications, and insulin injections. Before taking glyburide and metformin hydrochloride you should first try to control your diabetes by exercise and weight loss. Even if you are taking glyburide and metformin hydrochloride, you should still exercise and follow the diet recommended for your diabetes.

Q5. Does glyburide and metformin hydrochloride work differently from other glucose-control medications?

Yes, it does. Glyburide and metformin hydrochloride combines 2 glucose-lowering drugs, glyburide and metformin. These 2 drugs work together to improve the different metabolic defects found in type 2 diabetes. Glyburide lowers blood sugar primarily by causing more of the body’s own insulin to be released, and metformin lowers blood sugar, in part, by helping your body use your own insulin more effectively. Together, they are efficient in helping you to achieve better glucose control.

Q6. What happens if my blood sugar is still too high?

When blood sugar cannot be lowered enough by glyburide and metformin hydrochloride your doctor may prescribe injectable insulin or take other measures to control your diabetes.

Q7. Can glyburide and metformin hydrochloride cause side effects?

Glyburide and metformin hydrochloride, like all blood sugar-lowering medications, can cause side effects in some patients. Most of these side effects are minor. However, there are also serious, but rare, side effects related to glyburide and metformin hydrochloride (see Q9- Q13).

Q8. What are the most common side effects of glyburide and metformin hydrochloride?

The most common side effects of glyburide and metformin hydrochloride are normally minor ones such as diarrhea, nausea, and upset stomach. If these side effects occur, they usually occur during the first few weeks of therapy. Taking your glyburide and metformin hydrochloride with meals can help reduce these side effects.

Less frequently, symptoms of hypoglycemia (low blood sugar), such as lightheadedness, dizziness, shakiness, or hunger may occur. The risk of hypoglycemic symptoms increases when meals are skipped, too much alcohol is consumed, or heavy exercise occurs without enough food. Following the advice of your doctor can help you to avoid these symptoms.

Q9. Are there any serious side effects that glyburide and metformin hydrochloride can cause?

People who have a condition known as glucose-6-phosphate dehydrogenase (G6PD) deficiency and who take glyburide and metformin hydrochloride may develop hemolytic anemia (fast breakdown of red blood cells). G6PD deficiency usually runs in families. Tell your doctor if you or any members of your family have been diagnosed with G6PD deficiency before you start taking glyburide and metformin hydrochloride.

Glyburide and metformin hydrochloride rarely causes serious side effects. The most serious side effect that glyburide and metformin hydrochloride can cause is called lactic acidosis.

Q10. What is lactic acidosis and can it happen to me?

Metformin, one of the medicines in glyburide and metformin hydrochloride tablets can cause a rare but serious condition called lactic acidosis (a buildup of an acid in the blood) that can cause death. Lactic acidosis is a medical emergency and must be treated in the hospital.

Q11. Are there other risk factors for lactic acidosis?

Most people who have had lactic acidosis with metformin have other things that, combined with the metformin, led to the lactic acidosis. Tell your doctor if you have any of the following, because you have a higher chance for getting lactic acidosis with glyburide and metformin hydrochloride if you:

- have severe kidney problems, or your kidneys are affected by certain x-ray tests that use injectable dye
- have liver problems
- drink alcohol very often, or drink a lot of alcohol in short-term “binge” drinking
- get dehydrated (lose a large amount of body fluids). This can happen if you are sick with a fever, vomiting, or diarrhea. Dehydration can also happen when you sweat a lot with activity or exercise and do not drink enough fluids
- have surgery
- have a heart attack, severe infection, or stroke

The best way to keep from having a problem with lactic acidosis from metformin is to tell your doctor if you have any of the problems in the list above. Your doctor may decide to stop your glyburide and metformin hydrochloride for a while if you have any of these things.

Q12. What are the symptoms of lactic acidosis?

Call your doctor right away if you have any of the following symptoms, which could be signs of lactic acidosis:

- you feel cold in your hands or feet
- you feel dizzy or lightheaded
- you have a slow or irregular heartbeat
- you feel very weak or tired
- you have unusual (not normal) muscle pain
- you have trouble breathing
- you feel sleepy or drowsy
- you have stomach pains, nausea or vomiting

Q13. What does my doctor need to know to decrease my risk of lactic acidosis?

Before you take glyburide and metformin hydrochloride, tell your doctor if you:

- have severe kidney problems
- have liver problems
- have heart problems, including congestive heart failure
- drink alcohol very often, or drink a lot of alcohol in short term “binge” drinking
- are going to get an injection of dye or contrast agents for an x-ray procedure. Glyburide and metformin hydrochloride may need to be stopped for a short time. Talk to your doctor about when you should stop glyburide and metformin hydrochloride and when you should start glyburide and metformin hydrochloride again.
- have any other medical conditions

Q14. Can I take glyburide and metformin hydrochloride with other medications?

Remind your doctor that you are taking glyburide and metformin hydrochloride when any new drug is prescribed or a change is made in how you take a drug already prescribed. Glyburide and metformin hydrochloride may interfere with the way some drugs work and some drugs may interfere with the action of glyburide and metformin hydrochloride.

Do not take glyburide and metformin hydrochloride if you are taking bosentan used for pulmonary arterial hypertension (PAH), which is high blood pressure in the vessels of the lungs.

Q15. What if I become pregnant while taking glyburide and metforminhydrochloride?

Tell your doctor if you plan to become pregnant or have become pregnant. As with other oral glucose-control medications, you should not take glyburide and metformin hydrochloride during pregnancy.

Usually your doctor will prescribe insulin while you are pregnant. As with all medications, you and your doctor should discuss the use of glyburide and metformin hydrochloride if you are nursing a child.

Q16. How do I take glyburide and metformin hydrochloride?

Your doctor will tell you how many glyburide and metformin hydrochloride tablets to take and how often. This should also be printed on the label of your prescription. You will probably be started on a low dose of glyburide and metformin hydrochloride and your dosage will be increased gradually until your blood sugar is controlled.

Q17. Where can I get more information about glyburide and metforminhydrochloride?

This leaflet is a summary of the most important information about glyburide and metformin hydrochloride. If you have any questions or problems, you should talk to your doctor or other healthcare provider about type 2 diabetes as well as glyburide and metformin hydrochloride and its side effects. There is also a leaflet (package insert) written for health professionals that your pharmacist can let you read.
For more information, call Rising Health, LLC at 1-833-395-6928.

Trademarks are the property of their respective owners.
Distributed by:

Rising Health, LLC

Saddle Brook, NJ 07663

Made in India

Code: TS/DRUGS/19/1993

Revised: 12/2017